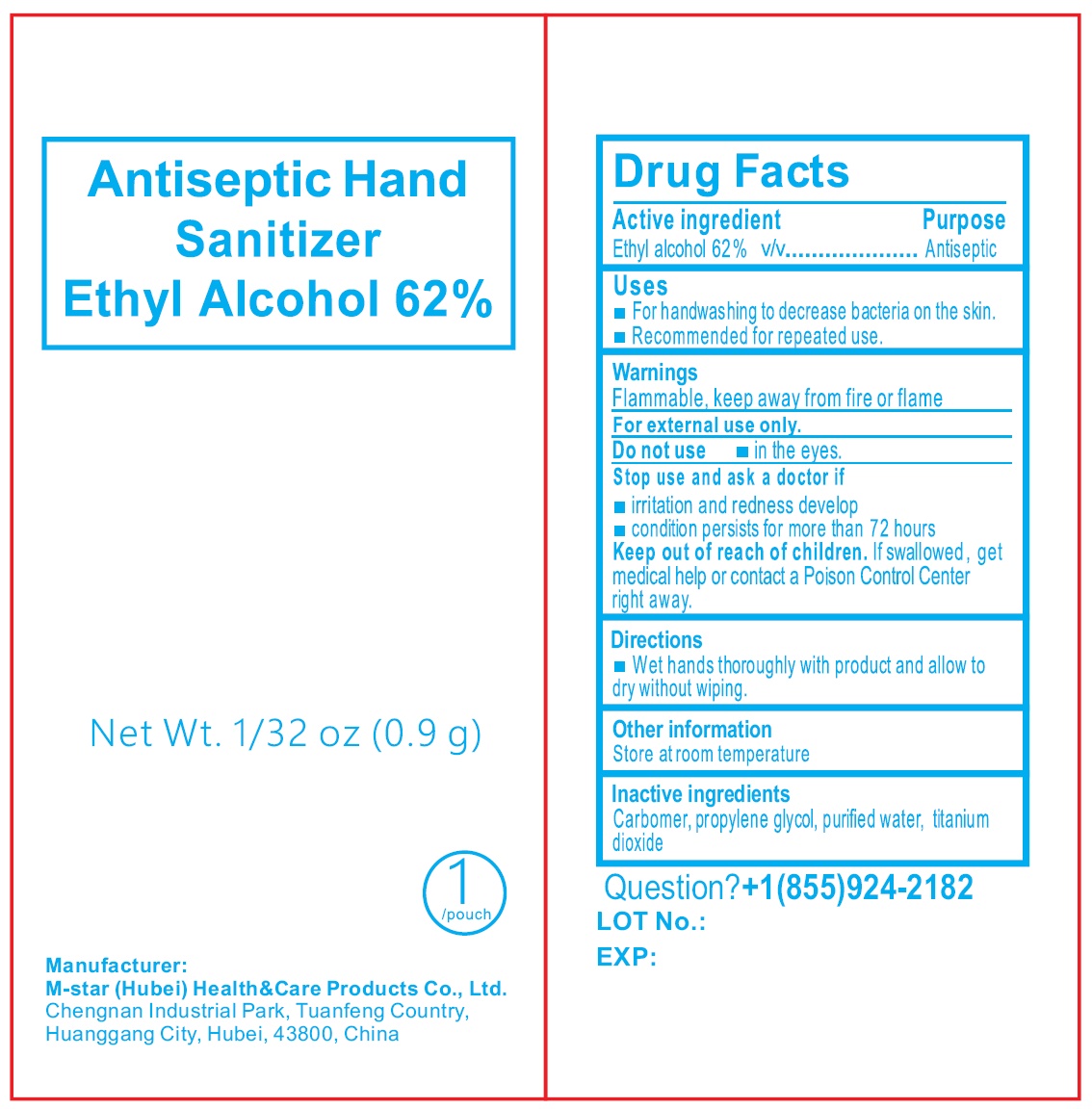 DRUG LABEL: Antiseptic Hand Sanitizer Ethyl Alcohol
NDC: 84219-005 | Form: LIQUID
Manufacturer: M-star (Hubei) Health&Care Products Co., Ltd.
Category: otc | Type: HUMAN OTC DRUG LABEL
Date: 20240401

ACTIVE INGREDIENTS: ALCOHOL 62 g/100 g
INACTIVE INGREDIENTS: CARBOMER HOMOPOLYMER, UNSPECIFIED TYPE; PROPYLENE GLYCOL; WATER; TITANIUM DIOXIDE

Antiseptic Hand Sanitizer Ethyl Alcohol

Active ingredient

Ethyl alcohol 62% v/v

Purpose

Antiseptic

Uses

- For handwashing to decrease bacteria on the skin.
- Recommended for repeated use.

Warnings

Flammable, keep away from fire or flame

For external use only.

Do not use

- in the eyes.

Stop use and ask a doctor if

- irritation and redness develop
- condition persists for more than 72 hours

Keep out of reach of children.

If swallowed, get medical help or contact a Poison Control Center right away.

Directions

- Wet hands thoroughly with product and allow to dry without wiping.

Other information

Store at room temperature

Inactive ingredients

Carbomer, propylene glycol, purified water, titanium dioxide

Question?

+1(855)924-2182